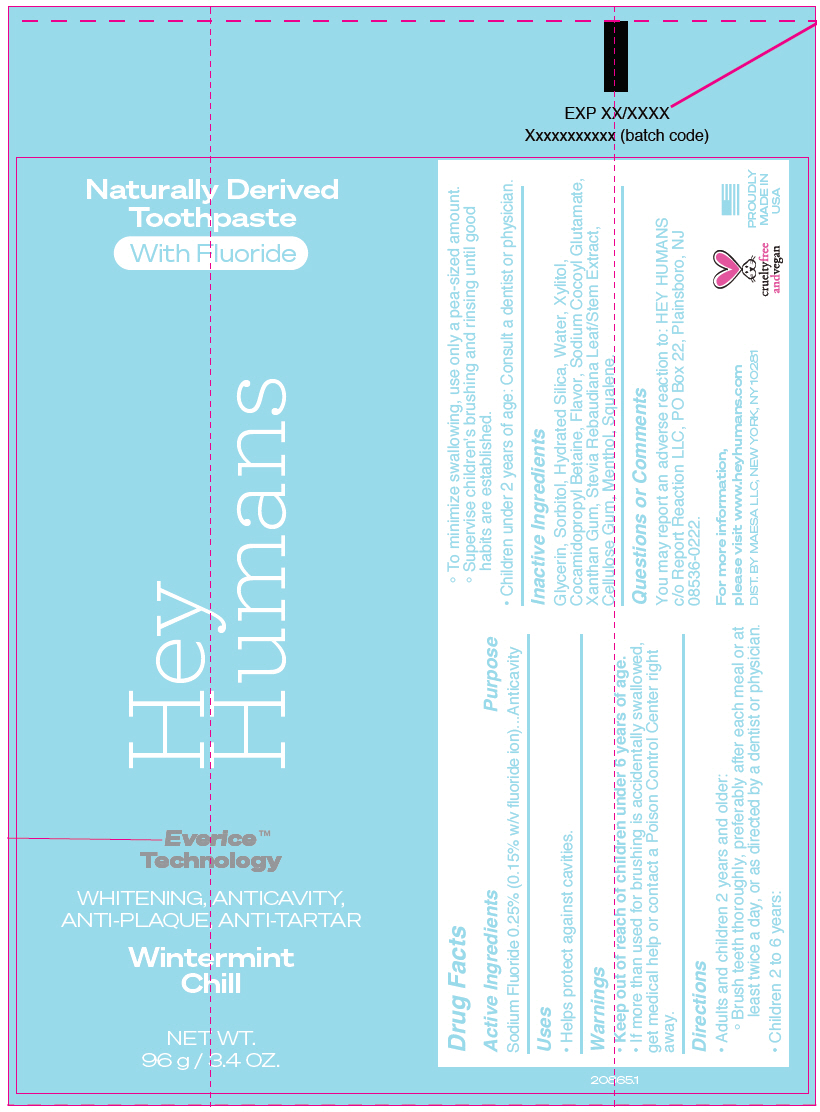 DRUG LABEL: Hey Humans Whitening Wintermint Chill
NDC: 71899-201 | Form: PASTE, DENTIFRICE
Manufacturer: Maesa LLC
Category: otc | Type: HUMAN OTC DRUG LABEL
Date: 20210301

ACTIVE INGREDIENTS: Sodium Fluoride 1.5 mg/1 g
INACTIVE INGREDIENTS: Glycerin; Sorbitol; Hydrated Silica; Water; Xylitol; Cocamidopropyl Betaine; Sodium Cocoyl Glutamate; Xanthan Gum; Stevia Rebaudiuna Leaf; Carboxymethylcellulose Sodium, Unspecified; Menthol, Unspecified Form; Squalene

Hey Humans Whitening Wintermint Chill

Drug Facts

Active Ingredients

Sodium Fluoride 0.25% (0.15% w/v fluoride ion)

Purpose

Anticavity

Uses

- Helps protect against cavities.

Warnings

- Keep out of reach of children under 6 years of age.
- If more than used for brushing is accidentally swallowed, get medical help or contact a Poison Control Center right away.

Directions

- Adults and children 2 years and older:
  - Brush teeth thoroughly, preferably after each meal or at least twice a day, or as directed by a dentist or physician.
- Children 2 to 6 years:
  - To minimize swallowing, use only a pea-sized amount.
  - Supervise children's brushing and rinsing until good habits are established.
- Children under 2 years of age: Consult a dentist or physician.

Inactive Ingredients

Glycerin, Sorbitol, Hydrated Silica, Water, Xylitol, Cocamidopropyl Betaine, Flavor, Sodium Cocoyl Glutamate, Xanthan Gum, Stevia Rebaudiana Leaf/Stem Extract, Cellulose Gum, Menthol, Squalene.

Questions or Comments

You may report an adverse reaction to: HEY HUMANS c/o Report Reaction LLC, PO Box 22, Plainsboro, NJ 08536-0222.

DIST. BY MAESA LLC, NEW YORK, NY 10281

PRINCIPAL DISPLAY PANEL - 96 g Tube Carton

Naturally Derived
Toothpaste

With Fluoride

Hey
Humans

Everice™
Technology

WHITENING, ANTICAVITY,
ANTI-PLAQUE, ANTI-TARTAR

Wintermint
Chill

NET WT.
96 g / 3.4 OZ.